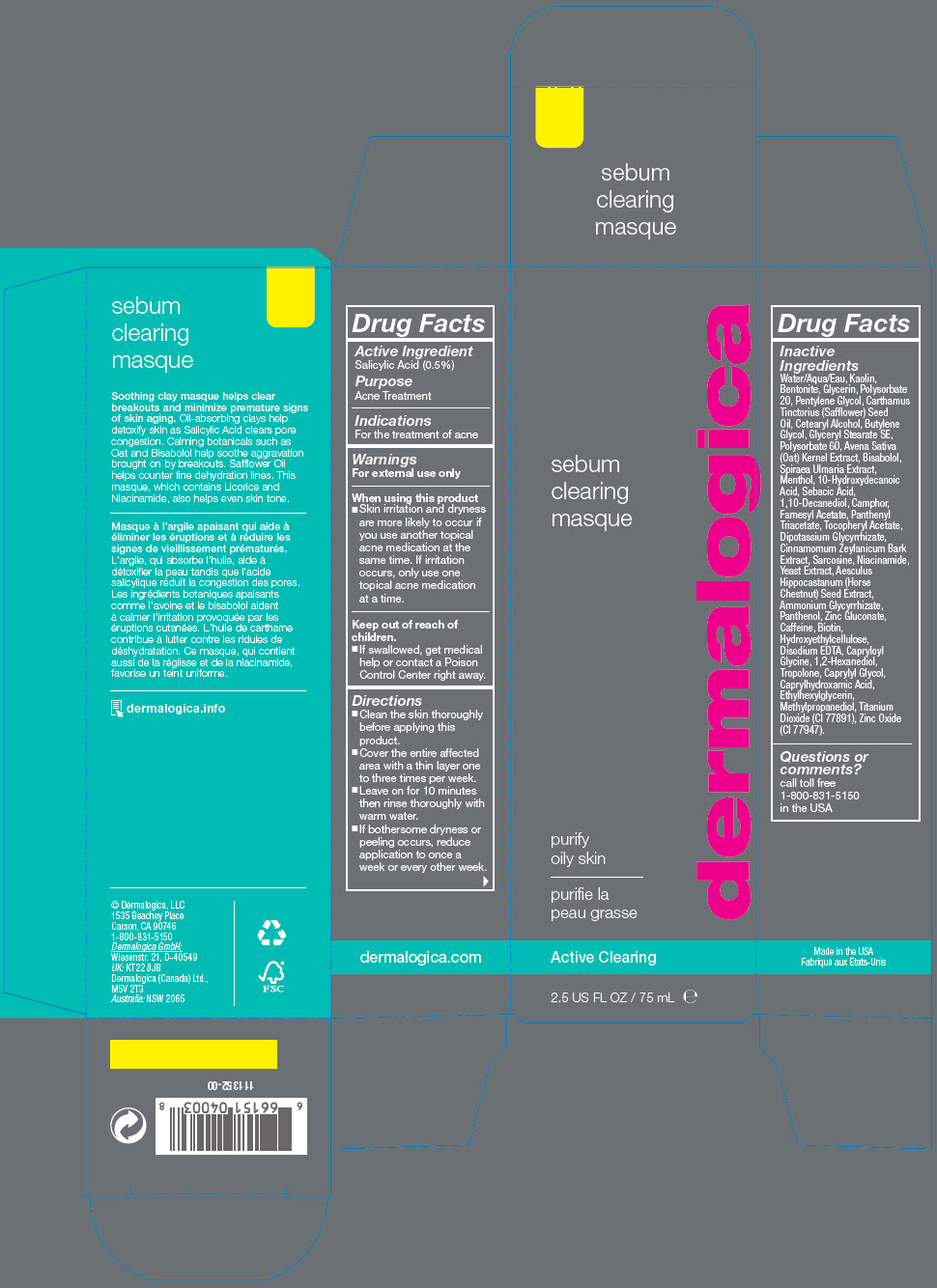 DRUG LABEL: Sebum Clearing Masque
NDC: 68479-013 | Form: LOTION
Manufacturer: Dermalogica
Category: otc | Type: HUMAN OTC DRUG LABEL
Date: 20220715

ACTIVE INGREDIENTS: Salicylic Acid 5 mg/1 mL
INACTIVE INGREDIENTS: Water; Kaolin; Bentonite; Glycerin; Polysorbate 20; Pentylene Glycol; Safflower Oil; Cetostearyl Alcohol; Butylene Glycol; Glyceryl Stearate SE; Polysorbate 60; Oat; Levomenol; Filipendula Ulmaria Root; Menthol, Unspecified Form; 10-Hydroxydecanoic Acid; Sebacic Acid; 1,10-Decanediol; Camphor (Synthetic); Farnesyl Acetate; Panthenol Triacetate, (+)-; .Alpha.-Tocopherol Acetate; Glycyrrhizinate Dipotassium; Cinnamon Bark Oil; Sarcosine; Niacinamide; Yeast, Unspecified; Horse Chestnut; Ammonium Glycyrrhizate; Panthenol; Zinc Gluconate; Caffeine; Biotin; Hydroxyethyl Cellulose (6500 MPA.S at 2%); Edetate Disodium; Capryloyl Glycine; 1,2-Hexanediol; Tropolone; Caprylyl Glycol; Caprylhydroxamic Acid; Ethylhexylglycerin; Methylpropanediol; Titanium Dioxide; Zinc Oxide

Sebum Clearing Masque

Drug Facts

Active Ingredient

Salicylic Acid (0.5%)

Purpose

Acne Treatment

Indications

For the treatment of acne

Warnings

For external use only

When using this product

- Skin irritation and dryness are more likely to occur if you use another topical acne medication at the same time. If irritation occurs, only use one topical acne medication at a time.

Keep out of reach of children.

- If swallowed, get medical help or contact a Poison Control Center right away.

Directions

- Clean the skin thoroughly before applying this product.
- Cover the entire affected area with a thin layer one to three times per week.
- Leave on for 10 minutes then rinse thoroughly with warm water.
- If bothersome dryness or peeling occurs, reduce application to once a week or every other week.

Inactive Ingredients

Water/Aqua/Eau, Kaolin, Bentonite, Glycerin, Polysorbate 20, Pentylene Glycol, Carthamus Tinctorius (Safflower) Seed Oil, Cetearyl Alcohol, Butylene Glycol, Glyceryl Stearate SE, Polysorbate 60, Avena Sativa (Oat) Kernel Extract, Bisabolol, Spiraea Ulmaria Extract, Menthol, 10-Hydroxydecanoic Acid, Sebacic Acid, 1,10-Decanediol, Camphor, Farnesyl Acetate, Panthenyl Triacetate, Tocopheryl Acetate, Dipotassium Glycyrrhizate, Cinnamomum Zeylanicum Bark Extract, Sarcosine, Niacinamide, Yeast Extract, Aesculus Hippocastanum (Horse Chestnut) Seed Extract, Ammonium Glycyrrhizate, Panthenol, Zinc Gluconate, Caffeine, Biotin, Hydroxyethylcellulose, Disodium EDTA, Capryloyl Glycine, 1,2-Hexanediol, Tropolone, Caprylyl Glycol, Caprylhydroxamic Acid, Ethylhexylglycerin, Methylpropanediol, Titanium Dioxide (CI 77891), Zinc Oxide (CI 77947).

Questions or comments?

call toll free 1-800-831-5150 in the USA

PRINCIPAL DISPLAY PANEL - 75 mL Tube Carton

sebum
clearing
masque

purify
oily skin

Active Clearing

2.5 US FL OZ / 75 mL ℮

dermalogica